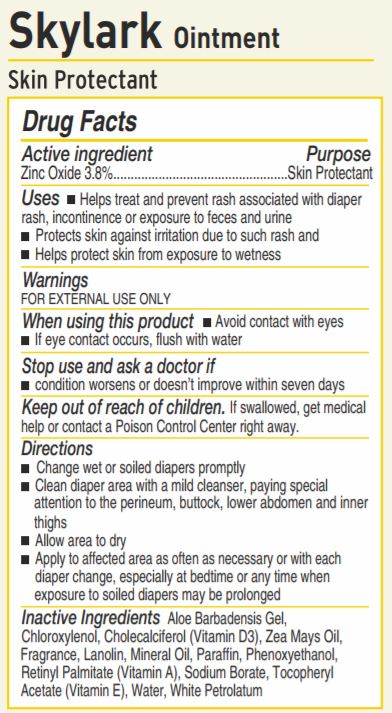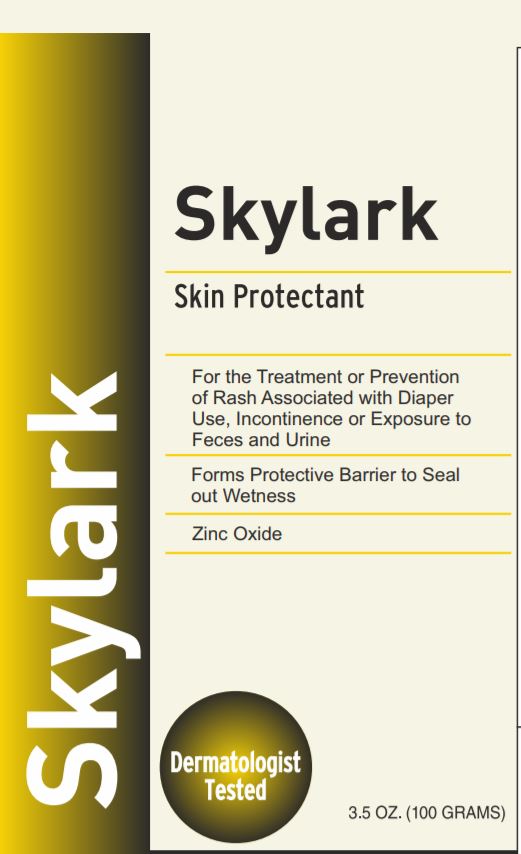 DRUG LABEL: SKYLARK
NDC: 71168-8020 | Form: OINTMENT
Manufacturer: Skylark CMC
Category: otc | Type: HUMAN OTC DRUG LABEL
Date: 20170908

ACTIVE INGREDIENTS: ZINC OXIDE 3.8 g/100 g
INACTIVE INGREDIENTS: SODIUM BORATE; ALPHA-TOCOPHEROL; PETROLATUM; CHLOROXYLENOL; CHOLECALCIFEROL; CORN OIL; LANOLIN; MINERAL OIL; PARAFFIN; PHENOXYETHANOL; VITAMIN A PALMITATE; WATER; ALOE VERA LEAF

Active ingredient

Zinc Oxide 3.8%

Purpose

Skin Protectant

Uses

- Helps treat and prevent rash associated with diaper rash, incontinence or exposure to feces and urine
- Protects skin against irritation due to such rash and
- Helps protect skin from exposure to wetness

Warnings

FOR EXTERNAL USE ONLY

When using this product

- Avoid contact with eyes
- if eye contact occurs, flush with water

Stop use and ask a doctor if

- condition worsens or doesn't improve within seven days

Keep out of reach of children

If swallowed get medical help or contact a Poison Control Center rightaway

Directions

- Change wet or soiled diapers promptly
- Clean diaper area with a mild cleanser, paying special attention to the perineum, buttocks, lower abdomen and inner thighs
- Allow area to dry
- Apply to affected area as often as necessary or with each diaper change, especially at bedtime or anytime when exposure to soiled diapers may be prolonged

Inactive Ingredients

Aloe Barbadensis Gel, Chloroxylenol, Cholecalciferol (Vitamin D3), Zea Mays Oil, Fragrance, Lanolin, Mineral Oil, Paraffin, Phenoxyethanol, Retinyl Palmitate (Vitamin A), Sodium Borate, Tocopherol Acetate (Vitamin E), Water, White Petrolatum